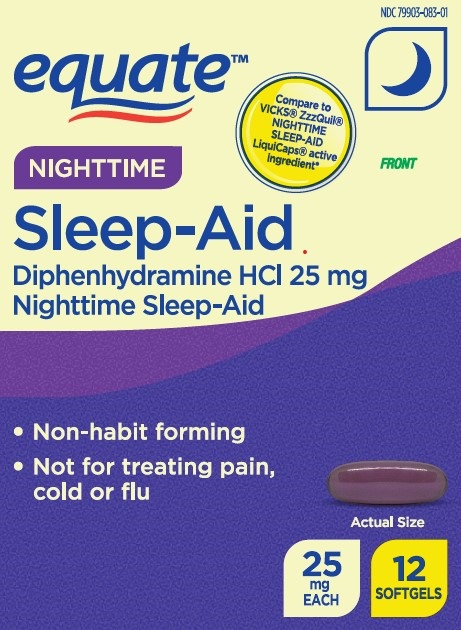 DRUG LABEL: NIGHTTIME SLEEP AID
NDC: 79903-083 | Form: CAPSULE, LIQUID FILLED
Manufacturer: Wal-Mart Stores Inc
Category: otc | Type: HUMAN OTC DRUG LABEL
Date: 20260127

ACTIVE INGREDIENTS: DIPHENHYDRAMINE HYDROCHLORIDE 25 mg/1 1
INACTIVE INGREDIENTS: FD&C BLUE NO. 1; FD&C RED NO. 40; GELATIN; GLYCERIN; POLYETHYLENE GLYCOL 400; PROPYLENE GLYCOL; SORBITOL; TITANIUM DIOXIDE; WATER

NIGHTTIME SLEEP-AID

Drug Facts

Active ingredients (in each softgel)

Diphenhydramine HCl 25 mg

Purpose

nighttime sleep-aid

Uses

- for the relief of occasional sleeplessness
- reduces time to fall asleep if you have difficulty falling asleep

Warnings

Do not use

- for children under 12 years of age
- with any other product containing diphenhydramine, even one used on skin.

Ask a doctor before use if you have

- a breathing problem such as asthma, emphysema, or chronic bronchitis
- glaucoma
- difficulty in urination due to enlargement of the prostate gland
- heart disease

Ask a doctor or pharmacist before use if you are taking sedatives, tranquilizers or any other sleep aid

When using this product

- avoid alcoholic beverages and other drugs that cause drowsiness
- drowsiness will occur
- be careful when driving a motor vehicle or operating machinery

Stop use and ask a doctor if sleeplessness persists continuously for more than 2 weeks. Insomnia may be a symptom of serious underlying medical illness.

PREGNANCY OR BREAST FEEDING

If pregnant or breast-feeding, ask a health professional before use.

Keep out of reach of children. Overdose warning: Taking more than directed can cause serious health problems. In case of overdose, get medical help or contact a Poison Control Center right away. 1(800)222-1222

Directions

- do not take more than directed
- take only one dose per day (24 hours)

adults & children 12 yrs & over | One dose=TWO 25 mg softgels (50 mg) at bed time if needed or as directed by a doctor
children under 12 years | Do not use

Other information

- store at 20-25°C (68-77°F)
- avoid excessive heat above 40°C (104°F) and high humidity
- Protect from light

Inactive ingredients

FD&C Blue#1, FD&C Red#40, gelatin, glycerin, polyethylene glycol-400, propylene glycol, sorbitol sorbitan, titanium dioxide

Questions or comments?

1-888-287-1915

DISPLAY PANEL

EQUATE

NIGHTTIME

SLEEP-AID

DIPHENHYDRAMINE HCl 25 mg

Non Habit-Forming

Not for Treating Pain, Cold or Flu